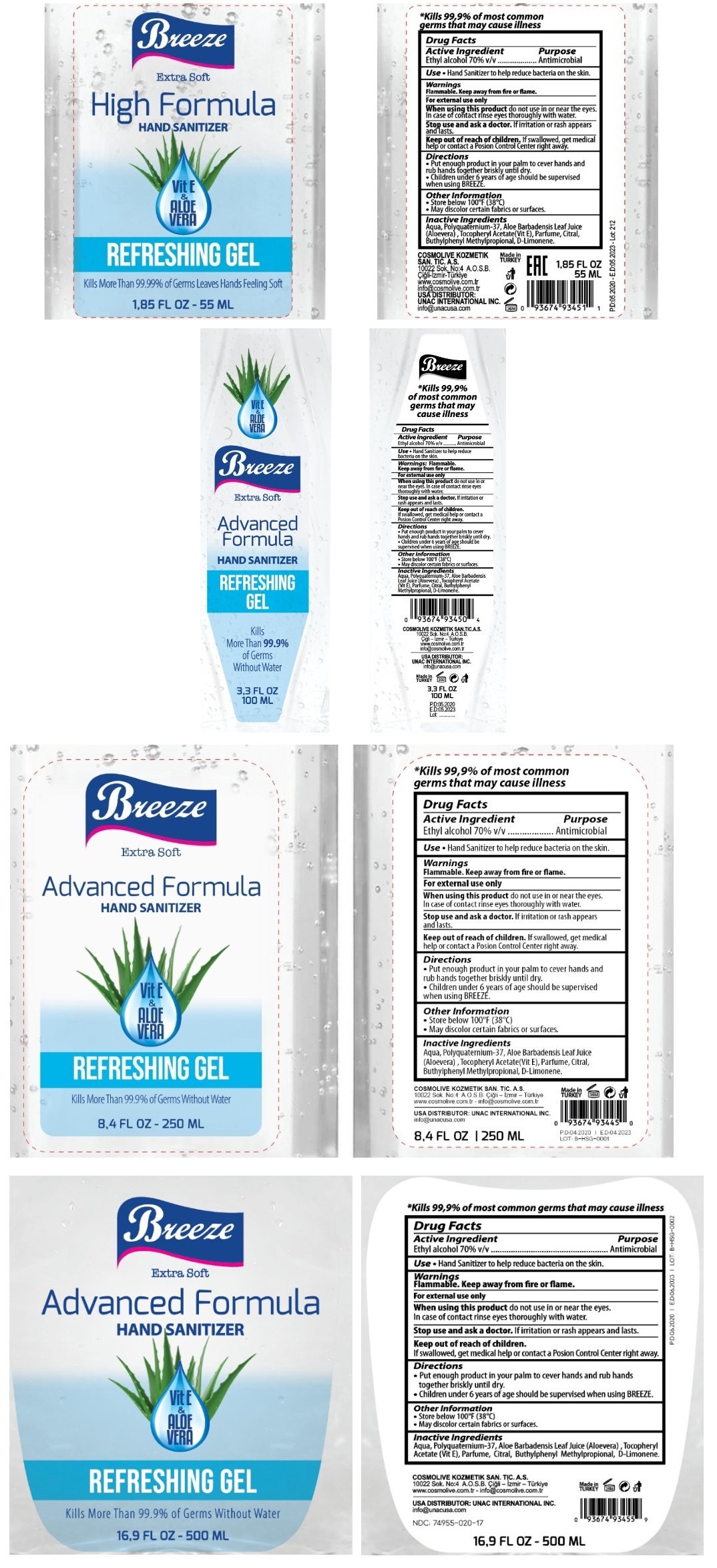 DRUG LABEL: Breeze Hand Sanitizer With Vitamin E and Aloe Vera
NDC: 74955-020 | Form: GEL
Manufacturer: COSMOLIVE KOZMETIK SANAYI VE TICARET ANONIM SIRKETI
Category: otc | Type: HUMAN OTC DRUG LABEL
Date: 20200605

ACTIVE INGREDIENTS: ALCOHOL 70 mL/100 mL
INACTIVE INGREDIENTS: WATER; POLYQUATERNIUM-37 (25000 MPA.S); ALOE VERA LEAF; .ALPHA.-TOCOPHEROL ACETATE; SULFURYL FLUORIDE; CITRAL; BUTYLPHENYL METHYLPROPIONAL; LIMONENE, (+)-

Breeze Advanced Formula Hand Sanitizer

Active Ingredient

Ethyl Alcohol 70% v/v

Purpose

Antimicrobial

INDICATIONS AND USAGE

Uses • Hand Sanitizer to help reduce bacteria on the skin.

Warnings

Flammable. Keep away from fire or flame.

For external use only

When using this product do not use in or near the eyes. In case of contact rinse eyes thoroughly with water.

Stop use and ask a doctor. If irritation or rashes appears and lasts.

Keep out of reach of children. If swallowed, get medical help or contact a Poison Control Center right away.

Directions

• Put enough product in your palm to cover hands and rub hands together briskly until dry.
• Children under 6 years of age should be supervised when using BREEZE.

Other Information

• Store below 100°F (38°C)
• May discolour certain fabrics or surfaces.

Inactive ingredients

Aqua, Polyquaternium-37, Aloe Barbadensis Leaf Juice (Aloevera), Tocopheryl Acetate(Vit E), Parfume, Citral, Butylphenyl Methylpropional, D-Limonene.

Extra Soft

Vit E & ALOE VERA

REFRESHING GEL

Kills More than 99.9% of Germs Without Water

*Kills 99.9% of most common germs that may cause illness

COSMOLIVE KOZMETIK SAN. TIC. A. S.

10022 Sok No: 4 A.O.S.B. Cigli- Izmir -Turkiye

www.cosmolive.com.tr - info@cosmolive.cpm.tr

USA DISTRIBUTOR: UNAC INTERNATIONAL INC.

info@unacusa.com

Made in TURKEY